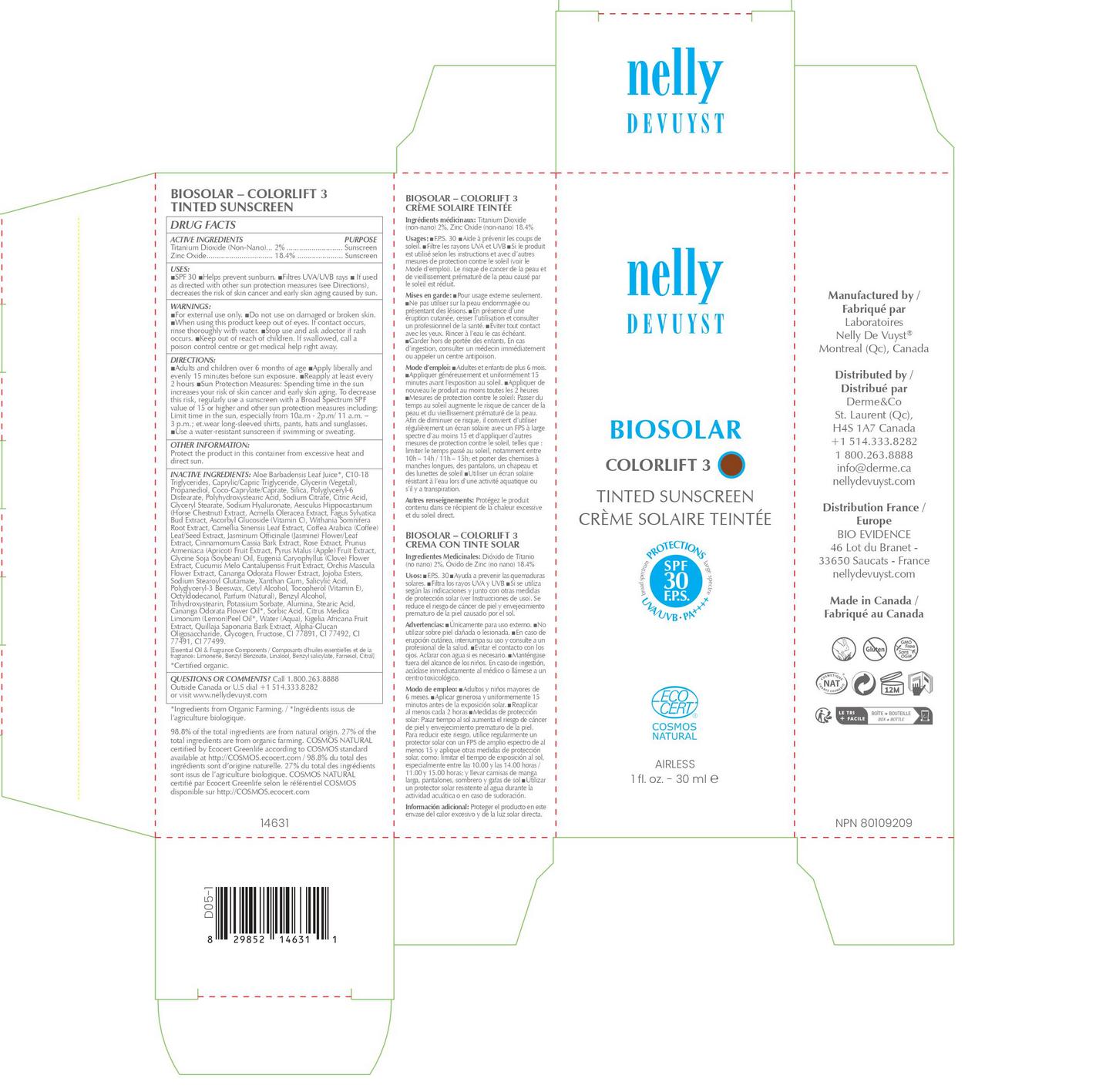 DRUG LABEL: NELLY DEVUYST BIOSOLAR COLORLIFT 3 TINTED SUNSCREEN
NDC: 71447-033 | Form: CREAM
Manufacturer: LABORATOIRES DRUIDE INC
Category: otc | Type: HUMAN OTC DRUG LABEL
Date: 20260114

ACTIVE INGREDIENTS: ZINC OXIDE 18.4 g/100 mL; TITANIUM DIOXIDE 2 g/100 mL
INACTIVE INGREDIENTS: GLYCOGEN; ALOE VERA LEAF; C10-18 TRIGLYCERIDES; MEDIUM-CHAIN TRIGLYCERIDES; GLYCERIN; PROPANEDIOL; COCO-CAPRYLATE/CAPRATE; SILICON DIOXIDE; POLYGLYCERYL-6 DISTEARATE; POLYHYDROXYSTEARIC ACID (2300 MW); SODIUM CITRATE; CITRIC ACID MONOHYDRATE; GLYCERYL MONOSTEARATE; HYALURONATE SODIUM; AESCULUS HIPPOCASTANUM SEED OIL; ACMELLA OLERACEA FLOWERING TOP; FAGUS SYLVATICA FLOWER BUD; ASCORBYL GLUCOSIDE; WITHANIA SOMNIFERA ROOT; CAMELLIA SINENSIS FLOWER; COFFEA ARABICA FRUIT; JASMINUM OFFICINALE LEAF; CINNAMOMUM CASSIA TWIG; ROSE OIL; PRUNUS ARMENIACA SEED; APPLE; SOYBEAN OIL; CLOVE; CANTALOUPE; ORCHIS MASCULA FLOWER; ALUMINUM OXIDE; JOJOBA OIL, RANDOMIZED; SALICYLIC ACID; FERRIC OXIDE RED; STEARIC ACID; CETYL ALCOHOL; KIGELIA AFRICANA FRUIT; .ALPHA.-GLUCAN OLIGOSACCHARIDE; FRUCTOSE; BENZYL ALCOHOL; WATER; FERROSOFERRIC OXIDE; CANANGA ODORATA FLOWER; SORBIC ACID; TOCOPHEROL; OCTYLDODECANOL; FRAGRANCE FRESH CITRUS FLORAL ORC1501495; XANTHAN GUM; LEMON OIL; POLYGLYCERIN-3; TRIHYDROXYSTEARIN; POTASSIUM SORBATE; CANANGA ODORATA LEAF OIL; QUILLAJA SAPONARIA BARK; FERRIC OXIDE YELLOW; SODIUM STEAROYL GLUTAMATE

NELLY DEVUYST BIOSOLAR COLORLIFT 3 TINTED SUNSCREEN SPF30 30mL

Active Ingredients

Titanium Dioxide (Non-Nano) 2%

Zinc Oxide 18.4%

Purpose

Sunscreen

Uses

▪ Helps prevent sunburn. ▪ If used as directed with other sun protection measures (see Directions), decreases the risk of skin cancer and early skin aging caused by the sun.

Warnings

For external use only

Do not use

on damaged or broken skin.

Stop use and ask a doctor if

rash occurs.

Keep out of reach of children

If swallowed, get medical help or contact Poison Control Center right away.

Directions

▪ Apply liberally and evenly 15 minutes before sun exposure ▪ Reapply ▪ After 80 minutes of swimming or sweating ▪ Immediately after towel drying ▪ At least every 2 hours ▪ Sun Protection Measures▪ Spending time in the sun increases your risk of skin cancer and early skin aging. To decrease this risk, regularly use a sunscreen with a Broad Spectrum SPF value of 15 or higher and other sun protection measures including: ▪ Limit time in the sun, especially from 10 a.m. - 2 p.m. ▪ Wear long-sleeved shirts, pants, hats, and sunglasses ▪ Use a water-resistant sunscreen if swimming or sweating.

Other Information

Protect the product in this container from excessive heat and direct sun.

Inactive Ingredients

Aloe Barbadensis Leaf Juice*, C10-18 Triglycerides, Caprylic/Capric Triglyceride, Glycerin (Vegetal), Propanediol, Coco-Caprylate/Caprate, Silica, Polyglyceryl-6 Distearate, Polyhydroxystearic Acid, Sodium Citrate, Citric Acid, Glyceryl Stearate, Sodium Hyaluronate, Aesculus Hippocastanum (Horse Chestnut) Extract, Acmella Oleracea Extract, Fagus Sylvatica Bud Extract, Ascorbyl Glucoside (Vitamin C), Withania Somnifera Root Extract, Camellia Sinensis Leaf Extract, Coffea Arabica (Coffee) Leaf/Seed Extract, Jasminum Officinale (Jasmine) Flower/Leaf Extract, Cinnamomum Cassia Bark Extract, Rose Extract, Prunus Armeniaca (Apricot) Fruit Extract, Pyrus Malus (Apple) Fruit Extract, Glycine Soja (Soybean) Oil, Eugenia Caryophyllus (Clove) Flower Extract, Cucumis Melo Cantalupensis Fruit Extract, Orchis Mascula Flower Extract, Cananga Odorata Flower Extract, Jojoba Esters, Sodium Stearoyl Glutamate, Xanthan Gum, Salicylic Acid, Polyglyceryl-3 Beeswax, Cetyl Alcohol, Tocopherol (Vitamin E), Octyldodecanol, Parfum (Natural), Benzyl Alcohol, Trihydroxystearin, Potassium Sorbate, Alumina, Stearic Acid, Cananga Odorata Flower Oil*, Sorbic Acid, Citrus Medica Limonum (Lemon) Peel Oil*, Water (Aqua), Kigelia Africana Fruit Extract, Quillaja Saponaria Bark Extract, Alpha-Glucan Oligosaccharide, Glycogen, Fructose, CI 77891, CI 77492, CI 77491, CI 77499.

*Certified organic.

Questions or Comments?

Call 1-800-263-8888
or visit www.nellydevuyst.com